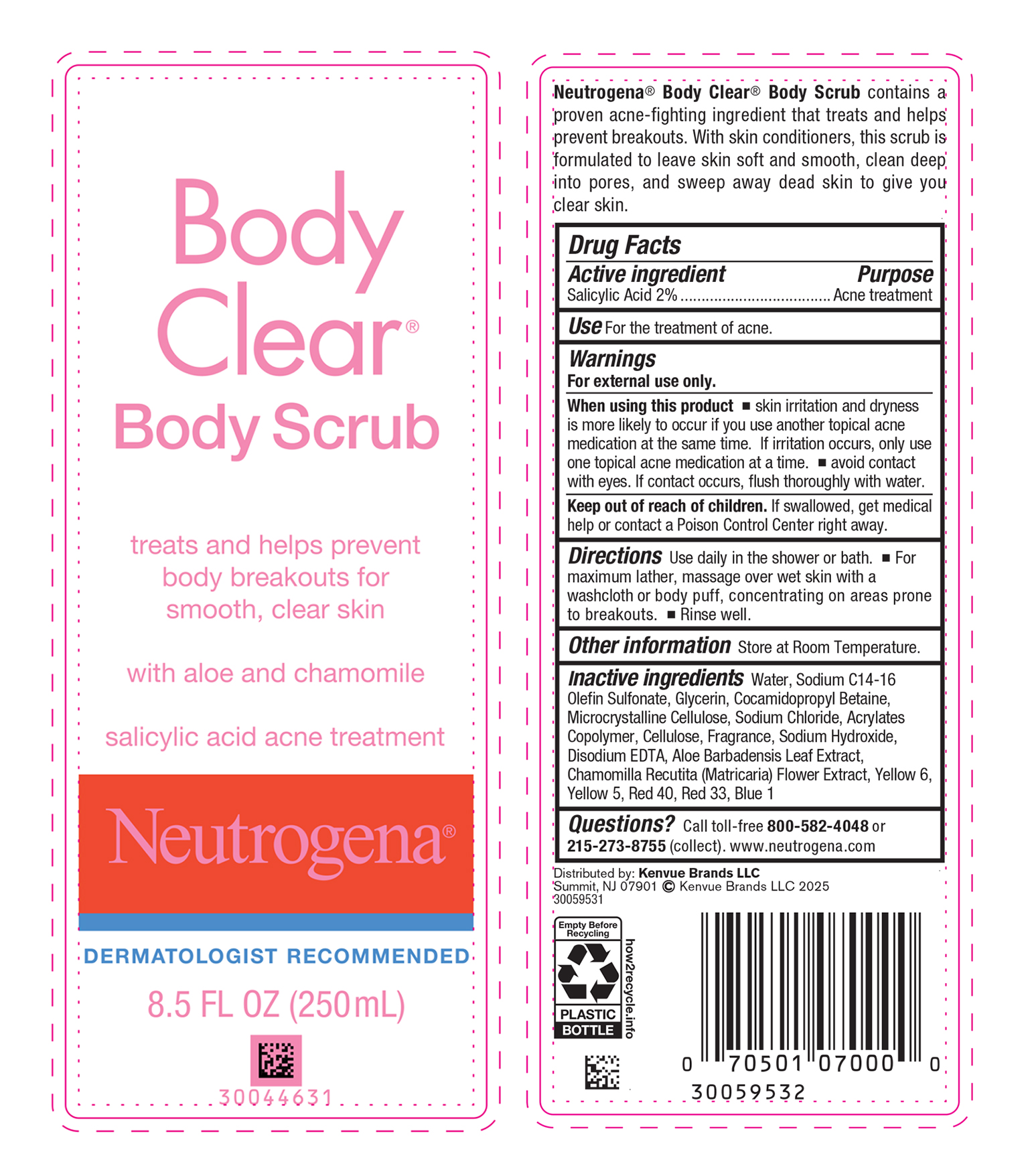 DRUG LABEL: Neutrogena Body Clear Body Scrub
NDC: 69968-0628 | Form: SUSPENSION
Manufacturer: Kenvue Brands LLC
Category: otc | Type: HUMAN OTC DRUG LABEL
Date: 20250320

ACTIVE INGREDIENTS: SALICYLIC ACID 20 mg/1 mL
INACTIVE INGREDIENTS: WATER; SODIUM C14-16 OLEFIN SULFONATE; GLYCERIN; COCAMIDOPROPYL BETAINE; MICROCRYSTALLINE CELLULOSE; SODIUM CHLORIDE; BUTYL ACRYLATE/METHYL METHACRYLATE/METHACRYLIC ACID COPOLYMER (18000 MW); POWDERED CELLULOSE; SODIUM HYDROXIDE; EDETATE DISODIUM ANHYDROUS; ALOE VERA LEAF; CHAMOMILE; FD&C YELLOW NO. 6; FD&C YELLOW NO. 5; FD&C RED NO. 40; D&C RED NO. 33; FD&C BLUE NO. 1

Neutrogena® Body Clear® Body Scrub

Drug Facts

Active ingredient

Salicylic Acid 2%

Purpose

Acne treatment

Use

For the treatment of acne.

Warnings

For external use only.

When using this product

- skin irritation and dryness is more likely to occur if you use another topical acne medication at the same time. If irritation occurs, only use one topical acne medication at a time.
- avoid contact with eyes. If contact occurs, flush thoroughly with water.

Keep out of reach of children. If swallowed, get medical help or contact a Poison Control Center right away.

Directions

Use daily in the shower or bath.

- For maximum lather, massage over wet skin with a washcloth or body puff, concentrating on areas prone to breakouts.
- Rinse well.

Other information

Store at Room Temperature.

Inactive ingredients

Water, Sodium C14-16 Olefin Sulfonate, Glycerin, Cocamidopropyl Betaine, Microcrystalline Cellulose, Sodium Chloride, Acrylates Copolymer, Cellulose, Fragrance, Sodium Hydroxide, Disodium EDTA, Aloe Barbadensis Leaf Extract, Chamomilla Recutita (Matricaria) Flower Extract, Yellow 6, Yellow 5, Red 40, Red 33, Blue 1

Questions?

Call toll-free 800-582-4048 or 215-273-8755 (collect). www.neutrogena.com

Distributed by:

Kenvue Brands LLC
Summit, NJ 07901

PRINCIPAL DISPLAY PANEL - 250 mL Bottle Label

Body
Clear®
Body Scrub

treats and helps prevent
body breakouts for
smooth, clear skin

with aloe and chamomile

salicylic acid acne treatment

Neutrogena®
DERMATOLOGIST RECOMMENDED

8.5 FL. OZ. (250 mL)